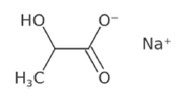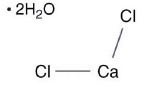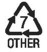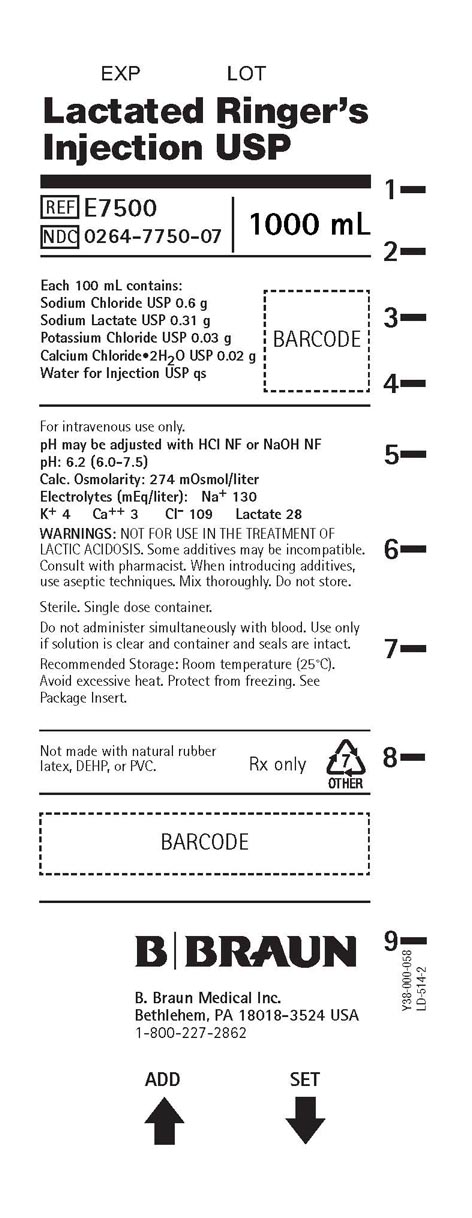 DRUG LABEL: Lactated Ringers
NDC: 0264-7750 | Form: INJECTION, SOLUTION
Manufacturer: B. Braun Medical Inc.
Category: prescription | Type: HUMAN PRESCRIPTION DRUG LABEL
Date: 20251105

ACTIVE INGREDIENTS: SODIUM CHLORIDE 0.6 g/100 mL; SODIUM LACTATE 0.31 g/100 mL; POTASSIUM CHLORIDE 0.03 g/100 mL; CALCIUM CHLORIDE 0.02 g/100 mL
INACTIVE INGREDIENTS: WATER

HIGHLIGHTS OF PRESCRIBING INFORMATION

These highlights do not include all the information needed to use LACTATED RINGER’S INJECTION safely and effectively. See full prescribing information for LACTATED RINGER’S INJECTION.
LACTATED RINGER’S injection, for intravenous use
Initial U.S. Approval: 1971

RECENT MAJOR CHANGES

Dosage and Administration (2.1, 2.2, 2.3, 2.4) 10/2025
Contraindications (4) 10/2025
Warnings and Precautions (5.1, 5.2, 5.3, 5.4, 5.5, 5.6, 5.7, 5.8, 5.9) 10/2025

1 INDICATIONS AND USAGE

Lactated Ringer’s Injection is indicated for use as a source of water and electrolytes or as an alkalinizing agent in adults and pediatric patients. (1)

2 DOSAGE AND ADMINISTRATION

- The recommended dosage and duration is based on the patient’s age, weight, clinical condition, and concomitant therapy. (2.1)
- To reduce the risk of air embolism, adhere to the preparation instructions. (2.2, 5.2)
- Lactated Ringer’s Injection is for intravenous use. (2.3)
- Instructions for Intravenous Administration of Plastic Container. (2.4)
- Do not administer Lactated Ringer’s Injection simultaneously with ceftriaxone in neonates (28 days of age or younger) due to serious risks. (2.5)
- See full prescribing information for information dosage considerations, preparation, administration, and drug incompatibilities. (2)

3 DOSAGE FORMS AND STRENGTHS

- Lactated Ringer’s Injection, USP 1000 mL for intravenous infusion (3)

4 CONTRAINDICATIONS

- Concomitant treatment with ceftriaxone in neonates (28 days of age or younger). (4)
- Patients with known hypersensitivity to any components of Lactated Ringer’s Injection. (4)

5 WARNINGS AND PRECAUTIONS

- Serious Risks with Inappropriate Use with Ceftriaxone: Deaths have occurred in neonates (28 days of age or younger) who received concomitant intravenous calcium-containing solutions with ceftriaxone. In patients older than 28 days, ceftriaxone and Lactated Ringer’s Injection may be administered sequentially if the infusion lines are thoroughly flushed between infusions. (4, 5.1, 8.4)
- Air Embolism: Use a non-vented infusion set or close the vent on a vented set and use a dedicated line without any connections. Pressure infusion is not recommended to increase flow rates, but if necessary, remove all air from the bag prior to initiating infusion. (5.2)
- Hypersensitivity Reactions: Stop the Lactated Ringer’s Injection infusion immediately if signs or symptoms of a hypersensitivity reaction develop. (5.3)
- Potassium Imbalances, Hyponatremia, Hypercalcemia, Fluid Overload, Acid-Base Imbalances, Interference with Interpretation of Serum Lactate Levels in Patients with Severe Metabolic Acidosis: See Full Prescribing Information for risk management recommendations. (5.4, 5.5, 5.6, 5.7, 5.8, 5.9)

6 ADVERSE REACTIONS

Common adverse reactions include infusion site reactions and symptoms of hypersensitivity reactions (e.g., pruritus, dyspnea, urticaria, rash, cough). (6)

To report SUSPECTED ADVERSE REACTIONS, contact B. Braun Medical Inc. at 1-833-425-1464 or FDA at 1-800-FDA-1088 or www.fda.gov/medwatch.

7 DRUG INTERACTIONS

- Drugs that Affect Electrolyte and/or Fluid Balance: Avoid concomitant use. If concomitant use cannot be avoided, closely monitor electrolyte concentrations and fluid balance. (7.1)
- Lithium: Avoid concomitant use. If concomitant use is unavoidable monitor serum lithium concentrations more frequently. (7.2)
- Digoxin: Consider reducing the volume or rate of Lactated Ringer’s Injection due to the increased risk of digoxin toxicity with calcium-containing solutions. (7.3)
- Drugs with pH-Dependent Renal Elimination: Renal clearance of acidic drugs may be increased. In contrast, renal clearance of alkaline drugs may be decreased. (7.4)

8 USE IN SPECIFIC POPULATIONS

- Closely monitor plasma electrolyte concentrations in young pediatric patients with immature kidney function. (8.4)
- Geriatric patients are more likely to have decreased renal function. Consider monitoring renal function and starting the infusion at the low end of the dosing range. (8.5)
- Avoid in patients with severe renal impairment. (8.6)
- Patients with severe hepatic impairment may have impaired lactate metabolism. Closely monitor serum lactate levels and acid-base status. (8.7)

FULL PRESCRIBING INFORMATION

1 INDICATIONS AND USAGE

Lactated Ringer’s Injection is indicated for use as a source of water and electrolytes or as an alkalinizing agent in adults and pediatric patients.

2 DOSAGE AND ADMINISTRATION

2.1 Dosage Considerations

The recommended dosage and duration of Lactated Ringer’s Injection is directed by a physician based on the patient’s age, weight, clinical condition, and concomitant therapy. Evaluate the patient’s clinical status and monitor changes in electrolyte concentrations especially during prolonged use of Lactated Ringer’s Injection to optimize clinical status.

2.2 Important Preparation Instructions

Visually inspect the Lactated Ringer’s Injection solution for particulate matter and discoloration. Do not administer Lactated Ringer’s Injection unless the solution is clear and the container and seals are intact.

If additives are determined to be compatible with Lactated Ringer’s Injection then using aseptic technique, mix thoroughly; do not store solutions containing additives. After mixing, do not use if there is discoloration or formation of precipitates.

To reduce the risk of air embolism, adhere to the following Lactated Ringer’s Injection preparation instructions [see Warnings and Precautions (5.2)]:

- Use a non-vented infusion set or close the vent on a vented set.
- Use a dedicated line without any connections (do not connect flexible containers in series).
- The use of pressure infusion is not recommended as a method to increase flow rates. However, if pressure infusion is required, ensure that any air within the bag is fully evacuated prior to initiation of infusion. If using a pumping device to administer Lactated Ringer’s Injection, turn off the pump before the container is empty.

Preparation Instructions
1. Check for minute leaks by squeezing solution container firmly. If leaks are found, discard solution as sterility may be impaired. If supplemental medication is desired, follow directions below before preparing for administration [see Dosage and Administration (2.3)].
2. Inspect each container. Read the label. Ensure solution is the one ordered and is within the expiration date.
3. Invert container and carefully inspect the solution in good light for cloudiness, haze, or particulate matter. Any container which is suspect should not be used.
4. If supplemental medication is desired, follow directions below [see Dosage and Administration (2.3)].

Preparation for Administration
1. Remove plastic protector from sterile set port at bottom of container.
2. Attach administration set according to its accompanying directions.

2.3 Important Administration Instructions

Lactated Ringer’s Injection is for intravenous use.

Use immediately after opening the container. Discard the unused portion. Some additives may be incompatible [see Dosage and Administration (2.4)].

To Add Medication Before Solution Administration
1. Prepare medication site by removing the additive port closure. Swab the exposed medication site before puncturing.
2. Using syringe with 18-22 gauge needle, puncture medication port and inner diaphragm and inject.
3. Squeeze and tap ports while ports are upright and mix solution and medication thoroughly.

To Add Medication During Solution Administration
1. Close clamp on the set.
2. Prepare medication site by removing the additive port closure. Swab the exposed medication site before puncturing.
3. Using syringe with 18-22 gauge needle of appropriate length (at least 5/8 inch), puncture resealable medication port and inner diaphragm and inject.
4. Remove container from IV pole and/or turn to an upright position.
5. Evacuate both ports by tapping and squeezing them while container is in the upright position.
6. Mix solution and medication thoroughly.
7. Return container to in use position and continue administration.

2.4 Drug Incompatibilities

Do not administer Lactated Ringer’s Injection simultaneously with ceftriaxone in neonates (28 days of age or younger) due to serious risks [see Contraindications (4) and Warnings and Precautions (5.1)]. However, in patients older than 28 days, ceftriaxone and Lactated Ringer’s Injection may be administered sequentially if the infusion lines are thoroughly flushed between infusions with a compatible fluid [see Warnings and Precautions (5.1)].

Do not administer Lactated Ringer’s Injection simultaneously with citrate anticoagulated/preserved blood through the same administration set because of the likelihood of coagulation precipitated by the calcium content of Lactated Ringer’s Injection.

3 DOSAGE FORMS AND STRENGTHS

Injection: Lactated Ringer’s Injection, USP as a clear, sterile, and nonpyrogenic solution packaged in a single-dose container: 1,000 mL.

4 CONTRAINDICATIONS

Lactated Ringer’s Injection, USP is contraindicated in:

- Neonates (28 days of age or younger) who are receiving concomitant treatment with ceftriaxone, even if separate infusion lines are used, due to the risk of fatal ceftriaxone-calcium salt precipitation in the neonate’s bloodstream [see Warnings and Precautions (5.1) and Specific Populations (8.4)].
- Patients with known hypersensitivity to any of the components of Lactated Ringer’s Injection [see Warnings and Precautions (5.3)].

5 WARNINGS AND PRECAUTIONS

5.1 Serious Risk with Concomitant Use with Ceftriaxone

Precipitation of ceftriaxone-calcium can occur when ceftriaxone is mixed with calcium-containing solutions, such as Lactated Ringer’s Injection, in the same intravenous administration line. Deaths have occurred in neonates (28 days of age or younger) who received concomitant intravenous calcium-containing solutions with ceftriaxone resulting from calcium-ceftriaxone precipitates in the lungs and kidneys, even when separate infusion lines were used:

Lactated Ringer’s Injection is contraindicated in neonates who receive ceftriaxone [see Contraindications (4), Use in Specific Populations (8.4)]. However, in patients older than 28 days, ceftriaxone and Lactated Ringer’s Injection may be administered sequentially if the infusion lines are thoroughly flushed between infusions with a compatible fluid.

5.2 Air Embolism

Cases of air embolism have been reported with pressurized administration of intravenous fluids. Air embolism may result in stroke, organ ischemia and/or infarction, and death.

Use a non-vented infusion set or close the vent on a vented set and use a dedicated line without any connections.

If administration is controlled by a pumping device, care must be taken to discontinue the pumping action before the container is empty.

Pressure infusion is not recommended to increase flow rates, but if necessary, ensure all air is removed from the bag before infusion.

Refrain from applying excessive pressure (>300mmHg) causing distortion to the container such as wringing or twisting. Such handling could result in breakage of the container [see Dosage and Administration (2.2)].

5.3 Hypersensitivity Reactions

Hypersensitivity reactions, including anaphylaxis and angioedema, have been reported with Lactated Ringer’s Injection. Stop the Lactated Ringer’s Injection infusion immediately and treat patient accordingly if signs or symptoms of a hypersensitivity reaction develop. Initiate appropriate treatment as clinically indicated.

5.4 Potassium Imbalances

Hyperkalemia

Potassium-containing solutions, including Lactated Ringer’s Injection, may increase the risk of hyperkalemia. This risk is increased in patients predisposed to hyperkalemia including those with severe renal impairment, acute dehydration, extensive tissue injury or burns, heart failure, or in those using concomitant drugs that are associated with hyperkalemia.

Avoid use of Lactated Ringer’s Injection in patients with, or at increased risk for, hyperkalemia. If use cannot be avoided in these patients, closely monitor serum potassium concentrations.

Hypokalemia

The potassium concentration in Lactated Ringer’s Injection is similar to the concentration in plasma. It is insufficient to normalize the serum potassium in patients with severe hypokalemia.

5.5 Hyponatremia

Lactated Ringer’s Injection may cause hyponatremia. Hyponatremia can lead to acute hyponatremic encephalopathy characterized by headache, nausea, seizures, lethargy and vomiting. The risk of hospital-acquired hyponatremia is increased in younger pediatric patients, geriatric patients, patients treated with diuretics, and patients with cardiac or pulmonary failure or with the syndrome of inappropriate antidiuretic hormone (SIADH) (e.g., postoperative patients, patients concomitantly treated with arginine vasopressin analogs, or certain antiepileptic, psychotropic, or cytotoxic drugs) [see Drug Interactions (7.1), Use in Specific Populations (8.4)].

Avoid Lactated Ringer’s Injection in patients with or at risk for hyponatremia. If use cannot be avoided in these patients, closely monitor serum sodium concentrations.

Rapid correction of hyponatremia may result in serious neurologic complications such as osmotic demyelination syndrome (ODS). To avoid complications, monitor serum sodium and chloride concentrations, fluid status, acid-base balance, and neurologic status.

5.6 Hypercalcemia

Lactated Ringer’s Injection contains calcium salts and may cause hypercalcemia. Avoid administration of Lactated Ringer’s Injection in patients with hypercalcemia, those with calcium-containing renal calculi or history of such calculi, those with conditions predisposing to hypercalcemia, or treated with concomitant thiazide diuretics or vitamin D.

5.7 Fluid Overload

Depending on the administered volume and the infusion rate, administration of Lactated Ringer’s Injection can cause fluid overload, including pulmonary edema.

Avoid Lactated Ringer’s Injection in patients at risk for fluid and/or solute overload including patients with severe renal impairment. If use cannot be avoided in these patients, monitor fluid balance, electrolyte concentrations and acid base balance, especially during prolonged use.

5.8 Acid/Base Imbalances

Because lactate is metabolized to bicarbonate, administration of Lactated Ringer’s Injection may result in, or worsen, metabolic alkalosis. Closely monitor the acid-base balance in patients with, or at risk of, alkalosis.

In patients with severe hepatic impairment, decreased lactate metabolism may result in worsening anion gap metabolic acidosis. Avoid Lactated Ringer’s Injection in patients with severe hepatic impairment. If use cannot be avoided in these patients, closely monitor serum bicarbonate levels.

5.9 Interference of Lactated Ringer’s Injection with Interpretation of Serum Lactate Levels in Patients with Severe Metabolic Acidosis

Administration of Lactated Ringer’s Injection may result in interference with the interpretation of serum lactate levels in patients with severe metabolic acidosis [see Drug Interactions (7.5)].

6 ADVERSE REACTIONS

The following serious adverse reactions are discussed in greater detail in other sections of the labeling:

• Serious Risk with Concomitant Use with Ceftriaxone [see Warnings and Precautions (5.1)]

• Air Embolism [see Warnings and Precautions (5.2)]

• Hypersensitivity Reactions [see Warnings and Precautions (5.3)]

• Potassium Imbalances [see Warnings and Precautions (5.4)]

• Hyponatremia [see Warnings and Precautions (5.5)]

• Hypercalcemia [see Warnings and Precautions (5.6)]

• Fluid Overload [see Warnings and Precautions (5.7)]

• Acid/Base Imbalances [see Warnings and Precautions (5.8)]

The following adverse reactions have been identified during postapproval use of Lactated Ringer’s Products. Because these reactions are reported voluntarily from a population of uncertain size, it is not always possible to reliably estimate their frequency or establish a causal relationship to drug exposure:

General Disorders and Administration Site Conditions:

Phlebitis, extravasation, infusion site inflammation, infusion site swelling, infusion site rash, infusion site pruritus, infusion site erythema, infusion site pain, infusion site burning, and infusion site hypoaesthesia.

Hypersensitivity Reactions and Infusion Reactions:

Angioedema, chest pain/discomfort, bradycardia or tachycardia, hypotension, respiratory distress, bronchospasm, dyspnea, cough, urticaria, rash, pruritus, erythema, flushing, throat irritation, paresthesia, oral hypoesthesia, dysgeusia, nausea, anxiety, pyrexia, headache, laryngeal edema, sneezing, and injection site infection.

Metabolism and Nutrition Disorders:

Hyperkalemia, hyponatremia, and hypervolemia.

Nervous System Disorders:

Hyponatremic encephalopathy.

7 DRUG INTERACTIONS

7.1 Drugs that Affect Electrolyte and/or Fluid Balance

Hyperkalemia

Administration of Lactated Ringer’s Injection to patients concomitantly treated or recently treated with drugs that are associated with hyperkalemia increases the risk of severe and potentially fatal hyperkalemia, especially in the presence of other hyperkalemia risk factors. Avoid use of Lactated Ringer’s Injection in patients receiving drugs that are associated with hyperkalemia (e.g., potassium-sparing diuretics, ACE inhibitors, angiotensin II receptor antagonists, or calcineurin inhibitors). If concomitant use cannot be avoided, closely monitor serum potassium concentrations during concomitant use [see Warnings and Precautions (5.4)].

Hyponatremia

Administration of Lactated Ringer’s Injection to patients treated concomitantly with drugs associated with hyponatremia may increase the risk of developing hyponatremia. These drugs include diuretics and those that cause SIADH (e.g. arginine vasopressin analogs, certain antiepileptic, psychotropic, or cytotoxic drugs). Avoid use of Lactated Ringer’s Injection in patients receiving such drugs. If use cannot be avoided, closely monitor serum sodium concentrations during concomitant use [see Warnings and Precautions (5.5)].

Hypercalcemia

Avoid the use of Lactated Ringer’s Injection in patients treated with thiazide diuretics or vitamin D because these drugs can increase the risk of hypercalcemia. If use cannot be avoided, closely monitor serum calcium concentrations during concomitant use [see Warnings and Precautions (5.6)].

Hypernatremia and Fluid Retention

Administration of Lactated Ringer’s Injection to patients treated concomitantly with drugs associated with sodium and fluid retention (e.g., corticosteroids or corticotropin) may increase the risk of hypernatremia and volume overload. Avoid use of Lactated Ringer’s Injection in patients receiving such drugs. If use cannot be avoided, closely monitor serum electrolytes, fluid balance, and acid-base balance during concomitant use.

7.2 Lithium

Renal sodium and lithium clearance may be increased during concomitant use of Lactated Ringer’s Injection and lithium and may result in decreased lithium concentrations. Avoid use of Lactated Ringer’s Injection in patients receiving lithium. If use cannot be avoided, increase the frequency of monitoring of serum lithium concentrations during concomitant use.

7.3 Digoxin

Administration of calcium via use of Lactated Ringer’s Injection may increase digoxin’s effects and lead to digoxin toxicity including serious or fatal cardiac arrhythmias. In digoxin-treated patients, consider reducing the volume and/or rate of Lactated Ringer’s Injection administration.

7.4 Drugs with pH-Dependent Renal Elimination

Due to the alkalinizing action of lactate (formation of bicarbonate), Lactated Ringer’s Injection may interfere with the elimination of drugs with pH-dependent renal elimination. Renal clearance of alkaline drugs may be decreased. In contrast, renal clearance of acidic drugs may be increased.

7.5 Interference of Lactated Ringer’s Injection with Interpretation of Serum Lactate Levels in Patients with Severe Metabolic Acidosis

Because administration of Lactated Ringer’s Injection may interfere with the interpretation of serum lactate levels in patients with severe metabolic acidosis, assessment of the patient’s clinical status should not solely rely on the measurement of serum lactate.

8 USE IN SPECIFIC POPULATIONS

8.1 Pregnancy

Risk Summary

Lactated Ringer’s as a source of water and electrolytes has been used for decades during labor and delivery. Although there are no reports of use of Lactated Ringer’s in other stages of pregnancy, exposure during pregnancy is not expected to cause major birth defects, miscarriage, or adverse maternal or fetal outcomes. Animal reproduction studies have not been conducted with this drug.

The background risk of major birth defects and miscarriage for the indicated population is unknown. All pregnancies have a background risk of birth defect, loss, or other adverse outcomes. In the U.S. general population, the estimated background risk of major birth defects and miscarriage in clinically recognized pregnancies is 2 to 4% and 15 to 20%, respectively.

8.2 Lactation

Risk Summary

Lactated Ringer’s as a source of water and electrolytes has been used for decades and is not expected to cause harm to a breastfed infant. There are no data on the presence of Lactated Ringer’s Injection in human milk, the effects on the breastfed infant, or the effects on milk production. The developmental and health benefits of breastfeeding should be considered along with the mother’s clinical need for Lactated Ringer’s Injection and any potential adverse effects on the breastfed infant from Lactated Ringer’s Injection or from the underlying maternal condition.

8.4 Pediatric Use

Lactated Ringer’s Injection is contraindicated in neonates (28 days of age or younger) who are receiving ceftriaxone due to reported deaths that occurred when neonates received ceftriaxone and intravenous calcium-containing solutions concomitantly [see Warnings and Precautions (5.1)].

The safety and effectiveness of Lactated Ringer’s Injection for use as a source of water and electrolytes or as an alkalinizing agent have been established in pediatric patients of all ages, including neonates.

Closely monitor plasma electrolyte concentrations in young pediatric patients with immature kidney function who may have decreased ability to maintain fluid and electrolyte balance [see Warnings and Precautions (5.4, 5.5, 5.8, 5.9)]. Administration of a lactate-containing intravenous solution, including Lactated Ringer’s Injection to pediatric patients should account for liver and kidney maturation (the kidney function affects the biotransformation and renal excretion of lactate) [see Warnings and Precautions (5.9)].

8.5 Geriatric Use

Geriatric patients treated with Lactated Ringer’s Injection are at increased risk of developing electrolyte imbalances. Lactated Ringer’s Injection is substantially excreted by the kidney, and the risk of adverse reactions to Lactated Ringer’s Injection may be greater in patients with renal impairment than in patients with normal renal function. Because geriatric patients are more likely to have decreased renal function, consider monitoring renal function in geriatric patients and consider starting the infusion at the low end of the dosing range.

8.6 Renal Impairment

Administration of Lactated Ringer’s Injection to patients with or at risk of severe renal impairment, may result in hyperkalemia and/or fluid overload [see Warnings and Precautions (5.4, 5.7, 5.9)]. Avoid Lactated Ringer’s Injection in patients with severe renal impairment. If use cannot be avoided in such patients, monitor for development of these adverse reactions.

8.7 Hepatic Impairment

In patients with severe hepatic impairment, lactate metabolism may be impaired and Lactated Ringer’s Injection may not produce alkalinization. Closely monitor serum lactate levels and acid-base status in such patients.

10 OVERDOSAGE

Excessive administration of Lactated Ringer’s Injection can cause:

- Hyperkalemia and hypernatremia, especially in patients with severe renal impairment.
- Fluid overload (which can lead to pulmonary and/or peripheral edema).
- Metabolic alkalosis with or without hypokalemia.
- Loss of bicarbonate with an acidifying effect
- Hypercalcemia

Overdose interventions include Lactated Ringer’s Injection discontinuation, treatment of hyperkalemia, and close monitoring of fluid balance, electrolyte concentrations, and acid-base balance [see Warnings and Precautions (5.4, 5.5, 5.6, 5.7, 5.8)].

11 DESCRIPTION

Lactated Ringer’s Injection, USP is a sterile, nonpyrogenic solution for fluid and electrolyte replenishment in a single-dose container intended for intravenous administration.

Composition, osmolarity, pH, ionic concentration and caloric content are shown in Table 1.

Table 1
 | Size (mL) | Composition (g/L) |  |  |  | Osmolarity [Normal physiologic osmolarity range is approximately 280 to 310 mOsmol/L.] (mOsmol/L) (calc) | pH [pH may be adjusted with Hydrochloric Acid NF or Sodium Hydroxide NF.] | Ionic Concentration (mEq/L) |  |  |  |  | Caloric Content (kcal/L)
 | Size (mL) | Sodium Chloride, USP | Sodium Lactate | Potassium Chloride, USP | Calcium Chloride, USP | Osmolarity [Normal physiologic osmolarity range is approximately 280 to 310 mOsmol/L.] (mOsmol/L) (calc) | pH [pH may be adjusted with Hydrochloric Acid NF or Sodium Hydroxide NF.] | Sodium | Potassium | Calcium | Chloride | Lactate | Caloric Content (kcal/L)
Lactated Ringer’s Injection, USP | 1000 | 6 | 3.1 | 0.3 | 0.2 | 274 | 6.2 (6.0 to 7.5) | 130 | 4 | 3 | 109 | 28 | 9

The chemical name, structural formula, and molecular weight of the active ingredients are shown in Table 2.

Table 2
The formulas of the active ingredients are:
Ingredients | Molecular Formula | Molecular Weight
Sodium Chloride USP | Na^+CI^− | 58.44
Sodium Lactate |  | 112.06
Potassium Chloride USP | K^+CI^− | 74.55
Calcium Chloride Dihydrate USP |  | 147.02

Not made with natural rubber latex, PVC or DEHP.

The plastic container is made from a homogenous blend of polypropylene and thermoplastic modifier developed for parenteral drugs. The container is a closed system and is not dependent upon entry of external air during administration.

The closure system has two ports; one for the administration set and the other is a medication addition site. Each port has a tamper evident cover [see Dosage and Administration (2.3)].

12 CLINICAL PHARMACOLOGY

12.1 Mechanism of Action

Lactated Ringer’s Injection is a source of water, electrolytes, and produces an alkalinizing effect.

- Sodium, the major cation of the extracellular fluid, functions primarily in the control of water distribution, fluid balance, and osmotic pressure of body fluids. Sodium is also associated with chloride and bicarbonate in the regulation of the acid-base equilibrium of body fluid.
- Potassium, the principal cation of intracellular fluid, participates in carbohydrate utilization and protein synthesis and is critical in the regulation of nerve conduction and muscle contraction, particularly in the heart.
- Chloride, the major extracellular anion, closely follows the metabolism of sodium, and changes in the acid-base balance of the body are reflected by changes in the chloride concentration.
- Calcium, an important cation, provides the framework of bones and teeth in the form of calcium phosphate and calcium carbonate. In the ionized form, calcium is essential for the functional mechanism of the clotting of blood, normal cardiac function, and regulation of neuromuscular irritability.
- Sodium lactate provides sodium and lactate ions. The lactate anion is in equilibrium with pyruvate and has an alkalinizing effect resulting from simultaneous removal by the liver of lactate and hydrogen ions. The sodium ion combines with bicarbonate ion produced from carbon dioxide of the body and thus retains bicarbonate to combat metabolic acidosis (bicarbonate deficiency).

12.2 Pharmacodynamics

The exposure-response relationship and time course of pharmacodynamic response for the safety and effectiveness of Lactated Ringer’s Injection have not been fully characterized.

12.3 Pharmacokinetics

Elimination

Metabolism/Excretion

Potassium: Normally about 80 to 90% of the potassium intake is excreted in the urine; the remainder is excreted in feces and to a smaller extent, in perspiration.

Sodium and Chloride: The distribution and excretion of sodium (Na+) and chloride (Cl−) are largely under the control of the kidney which maintains a balance between intake and output.

Lactate: In the liver, lactate is metabolized to carbon dioxide and water by oxidative metabolism and consumption of hydrogen cations.

13 NONCLINICAL TOXICOLOGY

13.1 Carcinogenesis, Mutagenesis, Impairment of Fertility

Carcinogenicity, genetic toxicology, and animal fertility studies have not been conducted with Lactated Ringer’s Injection.

16 HOW SUPPLIED/STORAGE AND HANDLING

How Supplied

Lactated Ringer’s Injection, USP is a clear, colorless solution packaged in a single-dose container.

Lactated Ringer’s Injection, USP is supplied sterile and nonpyrogenic in plastic containers packaged 12 per case.

It is available in the following presentation:

NDC | REF | Size
0264-7750-07 | E7500 | 1000 mL

Storage and Handling

Store at 20°C to 25°C (68°F to 77°F); excursions permitted between 15°C to 30°C (59°F to 86°F). [See USP Controlled Room Temperature.] Minimize exposure of Lactated Ringer’s Injection, USP to heat. Avoid excessive heat. Protect from freezing.

Rx only

B. Braun Medical Inc.

Bethlehem, PA 18018-3524 USA

1-800-227-2862

LD-513-4 Y36-003-094

PRINCIPAL DISPLAY PANEL - 1000 ML CONTAINER LABEL

Lactated Ringer’s
Injection USP

REF E7500

NDC 0264-7750-07

1000 mL

Each 100 mL contains:
Sodium Chloride USP 0.6 g
Sodium Lactate USP 0.31 g
Potassium Chloride USP 0.03 g
Calcium Chloride•2H2O USP 0.02 g
Water for Injection USP qs

For intravenous use only.

pH may be adjusted with HCl NF or NaOH NF
pH: 6.2 (6.0-7.5)
Calc. Osmolarity: 274 mOsmol/liter
Electrolytes (mEq/liter): Na^+ 130
K^+ 4 Ca^++ 3 Cl^- 109 Lactate 28

WARNINGS: NOT FOR USE IN THE TREATMENT OF
LACTIC ACIDOSIS. Some additives may be incompatible.
Consult with pharmacist. When introducing additives,
use aseptic techniques. Mix thoroughly. Do not store.

Sterile. Single dose container.

Do not administer simultaneously with blood. Use only
if solution is clear and container and seals are intact.

Recommended Storage: Room temperature (25°C).
Avoid excessive heat. Protect from freezing. See
Package Insert.

Not made with natural rubber
latex, DEHP, or PVC.

Rx only

B. Braun Medical Inc.
Bethlehem, PA 18018-3524 USA
1-800-227-2862

Y38-000-058
LD-514-2

ADD SET